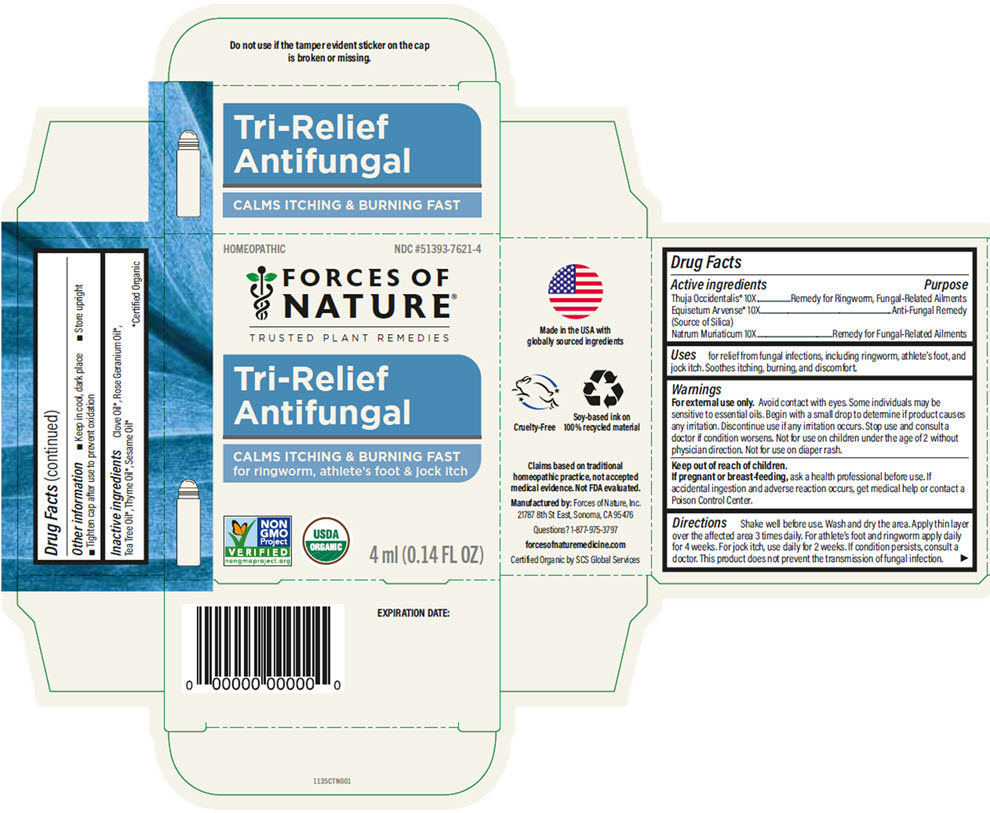 DRUG LABEL: Tri-Relief Antifungal
NDC: 51393-7621 | Form: SOLUTION/ DROPS
Manufacturer: Forces of Nature
Category: homeopathic | Type: HUMAN OTC DRUG LABEL
Date: 20251006

ACTIVE INGREDIENTS: SODIUM CHLORIDE 10 [hp_X]/100 mL; SILICON DIOXIDE 10 [hp_X]/100 mL; THUJA OCCIDENTALIS LEAFY TWIG 10 [hp_X]/100 mL
INACTIVE INGREDIENTS: SESAME OIL; TEA TREE OIL; PELARGONIUM GRAVEOLENS FLOWER OIL; THYME OIL; CLOVE OIL

Tri-Relief Antifungal

Drug Facts

ACTIVE INGREDIENT

Active ingredients | Purpose
Thuja Occidentalis 10X | Remedy for Ringworm, Fungal-Related Ailments
Equisetum Arvense 10X (Source of Silica) | Anti-Fungal Remedy
Natrum Muriaticum 10X | Remedy for Fungal-Related Ailments

Uses

for relief from fungal infections, including ringworm, athlete's foot, and jock itch. Soothes itching, burning, and discomfort.

Warnings

For external use only. Avoid contact with eyes. Some individuals may be sensitive to essential oils. Begin with a small drop to determine if product causes any irritation. Discontinue use if any irritation occurs. Stop use and consult a doctor if condition worsens. Not for use on children under the age of 2 without physician direction. Not for use on diaper rash.

Keep out of reach of children.

PREGNANCY OR BREAST FEEDING

If pregnant or breast-feeding, ask a health professional before use. If accidental ingestion and adverse reaction occurs, get medical help or contact a Poison Control Center.

Directions

Shake well before use. Wash and dry the area. Apply thin layer over the affected area 3 times daily. For athlete's foot and ringworm apply daily for 4 weeks. For jock itch, use daily for 2 weeks. If condition persists, consult a doctor. This product does not prevent the transmission of fungal infection.

Other information

- Keep in cool, dark place
- Store upright
- Tighten cap after use to prevent oxidation

Inactive ingredients

Clove Oil [Certified Organic] , Rose Geranium Oil, Tea Tree Oil, Thyme Oil, Sesame Oil

Questions?

1-877-975-3797

Manufactured by: Forces of Nature, Inc.
21787 8th St East, Sonoma, CA 95476

PRINCIPAL DISPLAY PANEL - 4 ml Bottle Carton

HOMEOPATHIC

NDC #51393-7621-4

FORCES OF
NATURE®
TRUSTED PLANT REMEDIES

Tri-Relief
Antifungal

CALMS ITCHING & BURNING FAST
for ringworm, athlete's foot & jock itch

NON
GMO
Project
VERIFIED
nongmoproject.org

USDA
ORGANIC

4 ml (0.14 FL OZ)